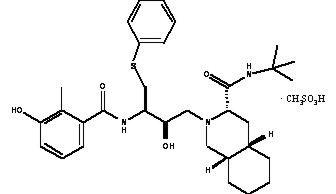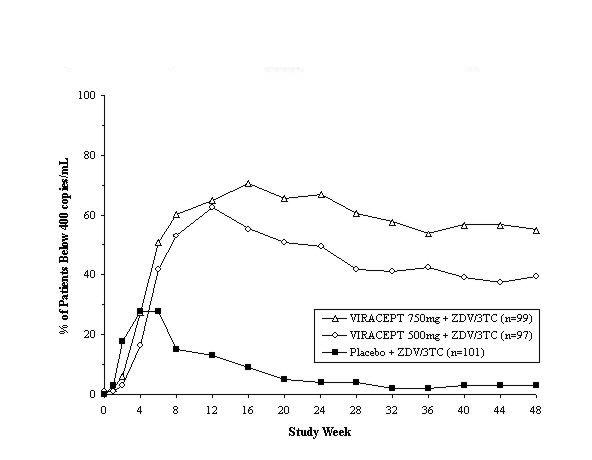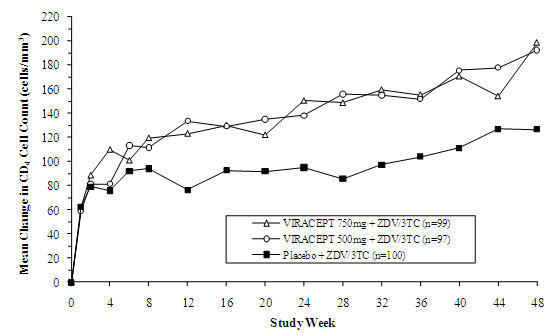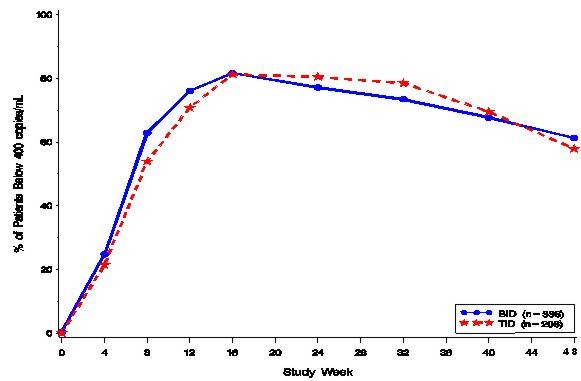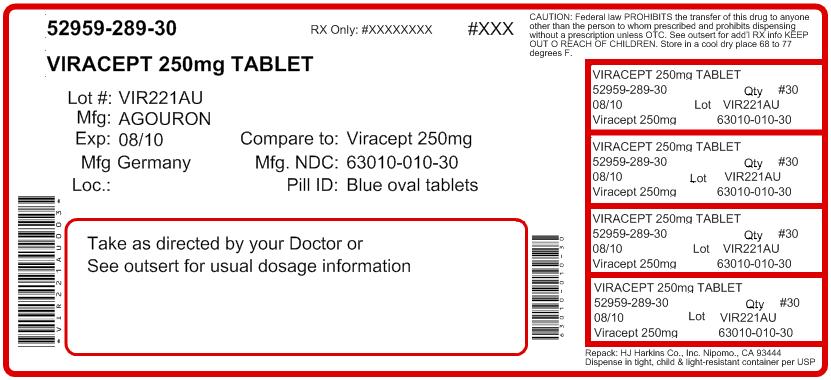 DRUG LABEL: VIRACEPT
                        
NDC: 52959-289 | Form: TABLET, FILM COATED
Manufacturer: H.J. Harkins Company, Inc.
Category: prescription | Type: HUMAN PRESCRIPTION DRUG LABEL
Date: 20120418

ACTIVE INGREDIENTS: nelfinavir mesylate 250 mg/1 1
INACTIVE INGREDIENTS: calcium silicate; crospovidone; magnesium stearate; hypromelloses; triacetin; FD&C blue No. 2

VIRACEPT®
(nelfinavir mesylate)
TABLETS and ORAL POWDER

DESCRIPTION

VIRACEPT® (nelfinavir mesylate) is an inhibitor of the human immunodeficiency virus (HIV) protease. VIRACEPT Tablets are available for oral administration as a light blue, capsule-shaped tablet with a clear film coating in 250 mg strength (as nelfinavir free base) and as a white oval tablet with a clear film coating in 625 mg strength (as nelfinavir free base). Each tablet contains the following common inactive ingredients: calcium silicate, crospovidone, magnesium stearate, hypromellose, and triacetin. In addition, the 250 mg tablet contains FD&C blue #2 powder and the 625 mg tablet contains colloidal silicon dioxide. VIRACEPT Oral Powder is available for oral administration in a 50 mg/g strength (as nelfinavir free base) in bottles. The oral powder also contains the following inactive ingredients: microcrystalline cellulose, maltodextrin, dibasic potassium phosphate, crospovidone, hypromellose, aspartame, sucrose palmitate, and natural and artificial flavor. The chemical name for nelfinavir mesylate is [3S-[2(2S*, 3S*), 3α,4aβ,8aβ]]-N-(1,1-dimethylethyl)decahydro-2-[2-hydroxy-3-[(3-hydroxy-2-methylbenzoyl)amino]-4-(phenylthio)butyl]-3-isoquinoline carboxamide mono-methanesulfonate (salt) and the molecular weight is 663.90 (567.79 as the free base). Nelfinavir mesylate has the following structural formula:

Nelfinavir mesylate is a white to off-white amorphous powder, slightly soluble in water at pH ≤4 and freely soluble in methanol, ethanol, 2-propanol and propylene glycol.

MICROBIOLOGY

Mechanism of Action

Nelfinavir is an inhibitor of the HIV-1 protease. Inhibition of the viral protease prevents cleavage of the gag and gag-pol polyprotein resulting in the production of immature, non-infectious virus.

Antiviral Activity In Vitro

The antiviral activity of nelfinavir in vitro has been demonstrated in both acute and/or chronic HIV infections in lymphoblastoid cell lines, peripheral blood lymphocytes and monocytes/macrophages. Nelfinavir was found to be active against several laboratory strains and clinical isolates of HIV-1 and the HIV-2 strain ROD. The EC95 (95% effective concentration) of nelfinavir ranged from 7 to 196 nM. Drug combination studies with protease inhibitors showed nelfinavir had antagonistic interactions with indinavir, additive interactions with ritonavir or saquinavir and synergistic interactions with amprenavir and lopinavir. Minimal to no cellular cytotoxicity was observed with any of these protease inhibitors alone or in combination with nelfinavir. In combination with reverse transcriptase inhibitors, nelfinavir demonstrated additive (didanosine or stavudine) to synergistic (abacavir, delavirdine, efavirenz, emtricitabine, lamivudine, nevirapine, tenofovir, zalcitabine or zidovudine) antiviral activity in vitro without enhanced cytotoxicity. Nelfinavir's anti-HIV activity was not antagonized by the anti-HCV drug ribavirin.

Drug Resistance

HIV-1 isolates with reduced susceptibility to nelfinavir have been selected in vitro. HIV isolates from selected patients treated with nelfinavir alone or in combination with reverse transcriptase inhibitors were monitored for phenotypic (n=19) and genotypic (n=195, 157 of which were evaluable) changes in clinical trials over a period of 2 to 82 weeks. One or more viral protease mutations at amino acid positions 30, 35, 36, 46, 71, 77 and 88 were detected in the HIV-1 of >10% of patients with evaluable isolates. The overall incidence of the D30N mutation in the viral protease of evaluable isolates (n=157) from patients receiving nelfinavir monotherapy or nelfinavir in combination with zidovudine and lamivudine or stavudine was 54.8%. The overall incidence of other mutations associated with primary protease inhibitor resistance was 9.6% for the L90M substitution whereas substitutions at 48, 82, or 84 were not observed. Of the 19 clinical isolates for which both phenotypic and genotypic analyses were performed, 9 showed reduced susceptibility (5- to 93-fold) to nelfinavir in vitro. All 9 patient isolates possessed one or more mutations in the viral protease gene. Amino acid position 30 appeared to be the most frequent mutation site.

Cross-resistance

Non-clinical Studies

Patient-derived recombinant HIV isolates containing the D30N mutation (n=4) and demonstrating high-level (>10-fold) NFV-resistance remained susceptible (<2.5-fold resistance) to amprenavir, indinavir, lopinavir, and saquinavir, in vitro. Patient-derived recombinant HIV isolates containing the L90M mutation (n=8) demonstrated moderate to high-level resistance to NFV and had varying levels of susceptibility to amprenavir, indinavir, lopinavir, and saquinavir, in vitro. Most patient-derived recombinant isolates with phenotypic and genotypic evidence of reduced susceptibility (>2.5-fold) to amprenavir, indinavir, lopinavir, and/or saquinavir demonstrated high-level cross-resistance to nelfinavir, in vitro. Mutations associated with resistance to other PIs (e.g. G48V, V82A/F/T, I84V, L90M) appeared to confer high-level cross-resistance to NFV. Following ritonavir therapy 6 of 7 clinical isolates with decreased ritonavir susceptibility (8- to 113-fold) in vitro compared to baseline also exhibited decreased susceptibility to nelfinavir in vitro (5- to 40-fold). Cross-resistance between nelfinavir and reverse transcriptase inhibitors is unlikely because different enzyme targets are involved. Clinical isolates (n=5) with decreased susceptibility to lamivudine, nevirapine or zidovudine remain fully susceptible to nelfinavir in vitro.

Clinical Studies

There have been no controlled or comparative studies evaluating the virologic response to subsequent protease inhibitor-containing regimens in patients who have demonstrated loss of virologic response to a nelfinavir-containing regimen. However, virologic response was evaluated in a single-arm prospective study of 26 patients with extensive prior antiretroviral experience with reverse transcriptase inhibitors (mean 2.9) who had received VIRACEPT for a mean duration of 59.7 weeks and were switched to a ritonavir (400 mg BID)/saquinavir hard-gel (400 mg BID) containing regimen after a prolonged period of VIRACEPT failure (median 48 weeks). Sequence analysis of HIV-1 isolates prior to switch demonstrated a D30N or an L90M substitution in 18 and 6 patients, respectively. Subjects remained on therapy for a mean of 48 weeks (range 40 to 56 weeks) where 17 of 26 (65%) subjects and 13 of 26 (50%) subjects were treatment responders with HIV RNA below the assay limit of detection (<500 HIV RNA copies/mL, Chiron bDNA) at 24 and 48 weeks, respectively.

CLINICAL PHARMACOLOGY

Pharmacokinetics

The pharmacokinetic properties of nelfinavir were evaluated in healthy volunteers and HIV-infected patients; no substantial differences were observed between the two groups.

Absorption

Pharmacokinetic parameters of nelfinavir (area under the plasma concentration-time curve during a 24-hour period at steady-state [AUC24], peak plasma concentrations [Cmax], morning and evening trough concentrations [Ctrough]) from a pharmacokinetic study in HIV-positive patients after multiple dosing with 1250 mg (five 250 mg tablets) twice daily (BID) for 28 days (10 patients) and 750 mg (three 250 mg tablets) three times daily (TID) for 28 days (11 patients) are summarized in Table 1.

Table 1 Summary of a Pharmacokinetic Study in HIV-positive Patients with Multiple Dosing of 1250 mg (five 250 mg tablets) BID for 28 days and 750 mg (three 250 mg tablets) TID for 28 days
Regimen | AUC24 mg.h/L | Cmax mg/L | Ctrough Morning mg/L | Ctrough Afternoon or Evening mg/L
1250 mg BID | 52.8 ± 15.7 | 4.0 ± 0.8 | 2.2 ± 1.3 | 0.7 ± 0.4
750 mg TID | 43.6 ± 17.8 | 3.0 ± 1.6 | 1.4 ± 0.6 | 1.0 ± 0.5
data are mean ± SD

The difference between morning and afternoon or evening trough concentrations for the TID and BID regimens was also observed in healthy volunteers who were dosed at precisely 8- or 12-hour intervals.

In healthy volunteers receiving a single 1250 mg dose, the 625 mg tablet was not bioequivalent to the 250 mg tablet formulation. Under fasted conditions (n=27), the AUC and Cmax were 34% and 24% higher, respectively, for the 625 mg tablets. In a relative bioavailability assessment under fed conditions (n=28), the AUC was 24% higher for the 625 mg tablet; the Cmax was comparable for both formulations. In HIV-1 infected subjects (N = 21) receiving multiple doses of 1250 mg BID under fed conditions, the 625 mg formulation was bioequivalent to the 250 mg formulation based on similarity in steady state exposure (Cmax and AUC).

Table 2 shows the summary of the steady state pharmacokinetic parameters (mean ± SD) of nelfinavir after multiple dose administration of 1250 mg BID (2 × 625 tablets) to HIV-infected patients (N = 21) for 14 days.

Table 2 Summary of the steady state pharmacokinetic parameters (mean ± SD) of nelfinavir after multiple dose administration of 1250 mg BID (2 × 625 tablets) to HIV-infected patients (N = 21) for 14 days.
Regimen | AUC12 mg.h/L | Cmax mg/L | Cmin mg/L
1250 mg BID | 35.3 (16.4) | 4.7 (1.9) | 1.5 (1.0)
AUC12: Steady state AUC
Cmax: Maximum plasma concentration at steady state
Cmin: Minimum plasma concentration at steady state

In healthy volunteers receiving a single 750 mg dose under fed conditions, nelfinavir concentrations were similar following administration of the 250 mg tablet and oral powder.

Effect of Food on Oral Absorption

Food increases nelfinavir exposure and decreases nelfinavir pharmacokinetic variability relative to the fasted state. In one study, healthy volunteers received a single dose of 1250 mg of VIRACEPT 250 mg tablets (5 tablets) under fasted or fed conditions (three different meals). In a second study, healthy volunteers received single doses of 1250 mg VIRACEPT (5 × 250 mg tablets) under fasted or fed conditions (two different fat content meals). The results from the two studies are summarized in Table 3 and Table 4, respectively.

Table 3 Increase in AUC, Cmax and Tmax for Nelfinavir in Fed State Relative to Fasted State Following 1250 mg VIRACEPT (5 × 250 mg tablets)
Number of Kcal | % Fat | Number of subjects | AUC fold increase | Cmax fold increase | Increase in Tmax (hr)
125 | 20 | n=21 | 2.2 | 2.0 | 1.00
500 | 20 | n=22 | 3.1 | 2.3 | 2.00
1000 | 50 | n=23 | 5.2 | 3.3 | 2.00

Table 4 Increase in Nelfinavir AUC, Cmax and Tmax in Fed Low Fat (20%) versus High Fat (50%) State Relative to Fasted State Following 1250 mg VIRACEPT (5 × 250 mg tablets)
Number of Kcal | % Fat | Number of subjects | AUC fold increase | Cmax fold increase | Increase in Tmax (hr)
500 | 20 | n=22 | 3.1 | 2.5 | 1.8
500 | 50 | n=22 | 5.1 | 3.8 | 2.1

Nelfinavir exposure can be increased by increasing the calorie or fat content in meals taken with VIRACEPT.

A food effect study has not been conducted with the 625 mg tablet. However, based on a cross-study comparison (n=26 fed vs. n=26 fasted) following single dose administration of nelfinavir 1250 mg, the magnitude of the food effect for the 625 mg nelfinavir tablet appears comparable to that of the 250 mg tablets. VIRACEPT should be taken with a meal.

Distribution

The apparent volume of distribution following oral administration of nelfinavir was 2–7 L/kg. Nelfinavir in serum is extensively protein-bound (>98%).

Metabolism

Unchanged nelfinavir comprised 82–86% of the total plasma radioactivity after a single oral 750 mg dose of ^14C-nelfinavir. In vitro, multiple cytochrome P-450 enzymes including CYP3A and CYP2C19 are responsible for metabolism of nelfinavir. One major and several minor oxidative metabolites were found in plasma. The major oxidative metabolite has in vitro antiviral activity comparable to the parent drug.

Elimination

The terminal half-life in plasma was typically 3.5 to 5 hours. The majority (87%) of an oral 750 mg dose containing ^14C-nelfinavir was recovered in the feces; fecal radioactivity consisted of numerous oxidative metabolites (78%) and unchanged nelfinavir (22%). Only 1–2% of the dose was recovered in urine, of which unchanged nelfinavir was the major component.

Special Populations

Hepatic Insufficiency

The steady-state pharmacokinetics of nelfinavir (1250 mg BID for 2 weeks) was studied in HIV-seronegative subjects with mild (Child-Pugh Class A; n=6) or moderate (Child-Pugh Class B; n=6) hepatic impairment. When compared with subjects with normal hepatic function, the Cmax and AUC of nelfinavir were not significantly different in subjects with mild hepatic impairment but were increased by 22% and 62%, respectively, in subjects with moderate hepatic impairment. The steady-state pharmacokinetics of nelfinavir has not been studied in HIV-seronegative subjects with severe hepatic impairment.

The steady-state pharmacokinetics of nelfinavir has not been studied in HIV-positive patients with any degree of hepatic impairment.

Renal Insufficiency

The pharmacokinetics of nelfinavir have not been studied in patients with renal insufficiency; however, less than 2% of nelfinavir is excreted in the urine, so the impact of renal impairment on nelfinavir elimination should be minimal.

Gender and Race

No significant pharmacokinetic differences have been detected between males and females. Pharmacokinetic differences due to race have not been evaluated.

Pediatrics

The pharmacokinetics of nelfinavir have been investigated in 5 studies in pediatric patients from birth to 13 years of age either receiving VIRACEPT three times or twice daily. The dosing regimens and associated AUC24 values are summarized in Table 5.

Table 5 Summary of Steady-state AUC24 of Nelfinavir in Pediatric Studies
Protocol no. | Dosing regimen [Protocol specified dose (actual dose range)] | N [N: number of subjects with evaluable pharmacokinetic results] | Age | AUC24 (mg.hr/L) arithmetic mean ± SD
AG1343-524 | 20 (19–28) mg/kg TID | 14 | 2–13 years | 56.1 ± 29.8
PACTG-725 | 55 (48–60) mg/kg BID | 6 | 3–11 years | 101.8 ± 56.1
PENTA 7 | 40 (34–43) mg/kg TID | 4 | 2–9 months | 33.8 ± 8.9
PENTA 7 | 75 (55–83) mg/kg BID | 12 | 2–9 months | 37.2 ± 19.2
PACTG-353 | 40 (14–56) mg/kg BID | 10 | 6 weeks | 44.1 ± 27.4
PACTG-353 | 40 (14–56) mg/kg BID | 10 | 1 week | 45.8 ± 32.1
Ctrough values are not presented in the table because they are not available for all studies

Pharmacokinetic data are also available for 86 patients (age 2 to 12 years) who received VIRACEPT 25–35 mg/kg TID in Study AG1343-556. The pharmacokinetic data from Study AG1343-556 were more variable than data from other studies conducted in the pediatric population; the 95% confidence interval for AUC24 was 9 to 121 mg.hr/L.

Overall, use of VIRACEPT in the pediatric population is associated with highly variable drug exposure. The high variability may be due to inconsistent food intake in pediatric patients. (See PRECAUTIONS: Pediatric Use, DOSAGE AND ADMINISTRATION.)

Geriatric Patients

The pharmacokinetics of nelfinavir have not been studied in patients over 65 years of age.

Drug Interactions

(also see CONTRAINDICATIONS, WARNINGS, PRECAUTIONS: Drug Interactions)

CYP3A and CYP2C19 appear to be the predominant enzymes that metabolize nelfinavir in humans. The potential ability of nelfinavir to inhibit the major human cytochrome P450 enzymes (CYP3A, CYP2C19, CYP2D6, CYP2C9, CYP1A2 and CYP2E1) has been investigated in vitro. Only CYP3A was inhibited at concentrations in the therapeutic range. Specific drug interaction studies were performed with nelfinavir and a number of drugs. Table 6 summarizes the effects of nelfinavir on the geometric mean AUC, Cmax and Cmin of coadministered drugs. Table 7 shows the effects of coadministered drugs on the geometric mean AUC, Cmax and Cmin of nelfinavir.

Table 6: Drug Interactions: Changes in Pharmacokinetic Parameters for Coadministered Drug in the Presence of VIRACEPT
 |  |  | % Change of Coadministered Drug Pharmacokinetic Parameters [↑ Indicates increase ↓ Indicates decrease ↔ Indicates no change (geometric mean exposure increased or decreased < 10%)] (90% CI)
Coadministered Drug | Nelfinavir Dose | N | AUC | Cmax | Cmin
HIV-Protease Inhibitors
Indinavir 800 mg Single Dose | 750 mg q8h × 7 days | 6 | ↑51% (↑29–↑77%) | ↓10% (↓28–↑13%) | NA
Ritonavir 500 mg Single Dose | 750 mg q8h × 5 doses | 10 | ↔ | ↔ | NA
Saquinavir 1200 mg Single Dose [Using the soft-gelatin capsule formulation of saquinavir 1200 mg] | 750 mg tid × 4 days | 14 | ↑392% (↑291–↑521%) | ↑179% (↑117–↑259%) | NA
Amprenavir 800 mg tid × 14 days | 750 mg tid × 14 days | 6 | ↔ | ↓14% (↓38–↑20%) | ↑189% (↑52–↑448%)
Nucleoside Reverse Transcriptase Inhibitors
Lamivudine 150 mg Single Dose | 750 mg q8h × 7–10 days | 11 | ↑10% (↑2–↑18%) | ↑31% (↑9–↑56%) | NA
Stavudine 30–40 mg bid × 56 days | 750 mg tid × 56 days | 8 | See footnote [Based on non-definitive cross-study comparison, drug plasma concentrations appeared to be unaffected by coadministration]
Zidovudine 200 mg Single Dose | 750 mg q8h × 7–10 days | 11 | ↓35% (↓29–↓40%) | ↓31% (↓13–↓46%) | NA
Non-Nucleoside Reverse Transcriptase Inhibitors
Efavirenz 600 mg qd × 7 days | 750 mg q8h × 7 days | 10 | ↓12% (↓31–↑12%) | ↓12% (↓29–↑8%) | ↓22% (↓54–↑32%)
Nevirapine 200 mg qd × 14 days Followed by 200 mg bid × 14 days | 750 mg tid × 36 days | 23 | See footnote
Delavirdine 400 mg q8h × 14 days | 750 mg q8h × 7 days | 7 | ↓31% (↓57–↑10%) | ↓27% (↓49–↑4%) | ↓33% (↓70–↑49%)
Anti-infective Agents
Rifabutin 150 mg qd × 8 days [Rifabutin 150 mg qd changes are relative to Rifabutin 300 mg qd × 8 days without coadministration with nelfinavir] | 750 mg q8h × 7–8 days [Comparable changes in rifabutin concentrations were observed with VIRACEPT 1250 mg q12h × 7 days] | 12 | ↑83% (↑72–↑96%) | ↑19% (↑11–↑28%) | ↑177% (↑144–↑215%)
Rifabutin 300 mg qd × 8 days | 750 mg q8h × 7–8 days | 10 | ↑207% (↑161–↑263%) | ↑146% (↑118–↑178%) | ↑305% (↑245–↑375%)
Azithromycin 1200 mg Single Dose | 750 mg tid × 11 days | 12 | ↑112% (↑80–↑150%) | ↑136% (↑77–↑215%) | NA
HMG-CoA Reductase Inhibitors
Atorvastatin 10 mg qd × 28 days | 1250 mg bid × 14 days | 15 | ↑74% (↑41–↑116%) | ↑122% (↑68–↑193%) | ↑39% (↓21–↑145%)
Simvastatin 20 mg qd × 28 days | 1250 mg bid × 14 days | 16 | ↑505% (↑393–↑643%) | ↑517% (↑367–↑715%) | ND
Other Agents
Ethinyl estradiol 35 µg qd × 15 days | 750 mg q8h × 7 days | 12 | ↓47% (↓42–↓52%) | ↓28% (↓16–↓37%) | ↓62% (↓57–↓67%)
Norethindrone 0.4 mg qd × 15 days | 750 mg q8h × 7 days | 12 | ↓18% (↓13–↓23%) | ↔ | ↓46% (↓38–↓53%)
Methadone 80 mg + / - 21 mg qd [Changes are reported for total plasma methadone; changes for the individual R-enantiomer and S-enantiomer were similar] > 1 month | 1250 mg bid × 8 days | 13 | ↓47% (↓42–↓51%) | ↓46% (↓42–↓49%) | ↓53% (↓49–↓57%)
Phenytoin 300 mg qd × 14 days [Phenytoin exposure measures are reported for total phenytoin exposure. The effect of nelfinavir on unbound phenytoin was similar] | 1250 mg bid × 7 days | 12 | ↓29% (↓17–↓39%) | ↓21% (↓12–↓29%) | ↓39% (↓27–↓49%)
NA: Not relevant for single-dose treatment; ND: Cannot be determined

Table 7: Drug Interactions: Changes in Pharmacokinetic Parameters for Nelfinavir in the Presence of the Coadministered Drug
 |  |  | % Change of Nelfinavir Pharmacokinetic Parameters [↑ Indicates increase ↓ Indicates decrease ↔ Indicates no change (geometric mean exposure increased or decreased < 10%)] (90% CI)
Coadministered Drug | Nelfinavir Dose | N | AUC | Cmax | Cmin
HIV-Protease Inhibitors
Indinavir 800 mg q8h × 7 days | 750 mg Single Dose | 6 | ↑83% (↑42–↑137%) | ↑31% (↑16–↑48%) | NA
Ritonavir 500 mg q12h × 3 doses | 750 mg Single Dose | 10 | ↑152% (↑96–↑224%) | ↑44% (↑28–↑63%) | NA
Saquinavir 1200 mg tid × 4 days [Using the soft-gelatin capsule formulation of saquinavir 1200 mg] | 750 mg Single Dose | 14 | ↑18% (↑7–↑30%) | ↔ | NA
Amprenavir 800 mg tid × 14 days | 750 mg tid × 14 days | 6 | See footnote [Based on non-definitive cross-study comparison, nelfinavir plasma concentrations appeared to be unaffected by coadministration]
Nucleoside Reverse Transcriptase Inhibitors
Didanosine 200 mg Single Dose | 750 mg Single Dose | 9 | ↔ | ↔ | NA
Zidovudine 200 mg + Lamivudine 150 mg Single Dose | 750 mg q8h × 7–10 days | 11 | ↔ | ↔ | ↔
Non-Nucleoside Reverse Transcriptase Inhibitors
Efavirenz 600 mg qd × 7 days | 750 mg q8h × 7 days | 7 | ↑20% (↑8–↑34%) | ↑21% (↑10–↑33%) | ↔
Nevirapine 200 mg qd × 14 days Followed by 200 mg bid × 14 days | 750 mg tid × 36 days | 23 | ↔ | ↔ | ↓32% (↓50–↑5%)
Delavirdine 400 mg q8h × 7 days | 750 mg q8h × 14 days | 12 | ↑107% (↑83–↑135%) | ↑88% (↑66–↑113%) | ↑136% (↑103–↑175%)
Anti-infective Agents
Ketoconazole 400 mg qd × 7 days | 500 mg q8h × 5–6 days | 12 | ↑35% (↑24–↑46%) | ↑25% (↑11–↑40%) | ↑14% (↓23–↑69%)
Rifabutin 150 mg qd × 8 days | 750 mg q8h × 7–8 days | 11 | ↓23% (↓14–↓31%) | ↓18% (↓8–↓27%) | ↓25% (↓8–↓39%)
Rifabutin 150 mg qd × 8 days | 1250 mg q12h × 7–8 days | 11 | ↔ | ↔ | ↓15% (↓43–↑27%)
Rifabutin 300 mg qd × 8 days | 750 mg q8h × 7–8 days | 10 | ↓32% (↓15–↓46%) | ↓24% (↓10–↓36%) | ↓53% (↓15–↓73%)
Rifampin 600 mg qd × 7 days | 750 mg q8h × 5–6 days | 12 | ↓83% (↓79–↓86%) | ↓76% (↓69–↓82%) | ↓92% (↓86–↓95%)
Azithromycin 1200 mg Single Dose | 750 mg tid × 9 days | 12 | ↓15% (↓7–↓22%) | ↓10% (↓19–↑1%) | ↓29% (↓19–↓38%)
HMG-CoA Reductase Inhibitors
Atorvastatin 10 mg qd × 28 days | 1250 mg bid × 14 days | 15 | See footnote
Simvastatin 20 mg qd × 28 days | 1250 mg bid × 14 days | 16 | See footnote
Other Agents
Methadone 80 mg + / - 21 mg qd > 1 month | 1250 mg bid × 8 days | 13 | See footnote
Phenytoin 300 mg qd × 7 days | 1250 mg bid × 14 days | 15 | ↔ | ↔ | ↓18% (↓45–↑23%)
Omeprazole 40 mg qd × 4 days administered 30 minutes before nelfinavir | 1250 mg bid × 4 days | 19 | ↓36% (↓20–↓49%) | ↓37% (↓23–↓49%) | ↓39% (↓15–↓57%)
NA: Not relevant for single-dose treatment

For information regarding clinical recommendations see CONTRAINDICATIONS, WARNINGS, PRECAUTIONS: Drug Interactions.

INDICATIONS AND USAGE

VIRACEPT in combination with other antiretroviral agents is indicated for the treatment of HIV infection.

Description of Studies

In the clinical studies described below, efficacy was evaluated by the percent of patients with plasma HIV RNA < 400 copies/mL (Studies 511 and 542) or < 500 copies/mL (Study ACTG 364), using the Roche RT-PCR (Amplicor) HIV-1 Monitor or < 50 copies/mL, using the Roche HIV-1 Ultrasensitive assay (Study Avanti 3). In the analysis presented in each figure, patients who terminated the study early for any reason, switched therapy due to inadequate efficacy or who had a missing HIV-RNA measurement that was either preceded or followed by a measurement above the limit of assay quantification were considered to have HIV-RNA above 400 copies/mL, above 500 copies/mL, or above 50 copies/mL at subsequent time points, depending on the assay that was used.

a. Studies in Antiretroviral Treatment Naive Patients

Study 511: VIRACEPT + zidovudine + lamivudine versus zidovudine + lamivudine

Study 511 was a double-blind, randomized, placebo-controlled trial comparing treatment with zidovudine (ZDV; 200 mg TID) and lamivudine (3TC; 150 mg BID) plus 2 doses of VIRACEPT (750 mg and 500 mg TID) to zidovudine (200 mg TID) and lamivudine (150 mg BID) alone in 297 antiretroviral naive HIV-1 infected patients (median age 35 years [range 21 to 63], 89% male and 78% Caucasian). Mean baseline CD4 cell count was 288 cells/mm^3 and mean baseline plasma HIV RNA was 5.21 log10 copies/mL (160,394 copies/mL). The percent of patients with plasma HIV RNA < 400 copies/mL and mean changes in CD4 cell count are summarized in Figures 1 and 2, respectively.

Figure 1
Study 511: Percentage of Patients With HIV RNA Below 400 Copies/mL

Figure 2
Study 511: Mean Change From Baseline in CD4 Cell Counts

Study 542: VIRACEPT BID + stavudine + lamivudine compared to VIRACEPT TID + stavudine + lamivudine

Study 542 is an ongoing, randomized, open-label trial comparing the HIV RNA suppression achieved by VIRACEPT 1250 mg BID versus VIRACEPT 750 mg TID in patients also receiving stavudine (d4T; 30–40 mg BID) and lamivudine (3TC; 150 mg BID). Patients had a median age of 36 years (range 18 to 83), were 84% male, and were 91% Caucasian. Patients had received less than 6 months of therapy with nucleoside transcriptase inhibitors and were naïve to protease inhibitors. Mean baseline CD4 cell count was 296 cells/mm^3 and mean baseline plasma HIV RNA was 5.0 log10 copies/mL (100,706 copies/mL).

Results showed that there was no significant difference in mean CD4 cell count among treatment groups; the mean increases from baseline for the BID and TID arms were 150 cells/mm^3 at 24 weeks and approximately 200 cells/mm^3 at 48 weeks.

The percent of patients with HIV RNA < 400 copies/mL is summarized in Figure 3. The outcomes of patients through 48 weeks of treatment are summarized in Table 8.

Figure 3

Study 542: Percentage of Patients With HIV RNA Below 400 Copies/mL

Table 8 Outcomes of Randomized Treatment Through 48 Weeks
Outcome | VIRACEPT 1250 mg BID Regimen | VIRACEPT 750 mg TID Regimen
Number of patients evaluable [Twelve patients in the BID arm and fourteen patients in the TID arm had not yet reached 48 weeks of therapy.] | 323 | 192
HIV RNA < 400 copies/mL | 198 (61%) | 111 (58%)
HIV RNA ≥ 400 copies/mL | 46 (14%) | 22 (11%)
Discontinued due to VIRACEPT toxicity [These rates only reflect dose-limiting toxicities that were counted as the initial reason for treatment failure in the analysis (see ADVERSE REACTIONS for a description of the safety profile of these regimens).] | 9 (3%) | 2 (1%)
Discontinued due to other antiretroviral agents' toxicity | 3 (1%) | 3 (2%)
Others [Consent withdrawn, lost to follow-up, intercurrent illness, noncompliance or missing data; all assumed as failures.] | 67 (21%) | 54 (28%)

Study Avanti 3: VIRACEPT TID + zidovudine + lamivudine compared to zidovudine + lamivudine

Study Avanti 3 was a placebo-controlled, randomized, double-blind study designed to evaluate the safety and efficacy of VIRACEPT (750 mg TID) in combination with zidovudine (ZDV; 300 mg BID) and lamivudine (3TC; 150 mg BID) (n=53) versus placebo in combination with ZDV and 3TC (n=52) administered to antiretroviral-naive patients with HIV infection and a CD4 cell count between 150 and 500 cells/µL. Patients had a mean age of 35 (range 22–59), were 89% male, and 88% Caucasian. Mean baseline CD4 cell count was 304 cells/mm^3 and mean baseline plasma HIV RNA was 4.8 log10 copies/mL (57,887 copies/mL). The percent of patients with plasma HIV RNA < 50 copies/mL at 52 weeks was 54% for the VIRACEPT + ZDV + 3TC treatment group and 13% for the ZDV + 3TC treatment group.

b. Studies in Antiretroviral Treatment Experienced Patients

Study ACTG 364: VIRACEPT TID + 2NRTIs compared to efavirenz + 2NRTIs compared to VIRACEPT + efavirenz + 2NRTIs

Study ACTG 364 was a randomized, double-blind study that evaluated the combination of VIRACEPT 750 mg TID and/or efavirenz 600 mg QD with 2 NRTIs (either didanosine [ddI] + d4T, ddI + 3TC, or d4T + 3TC) in patients with prolonged prior nucleoside exposure who had completed 2 previous ACTG studies. Patients had a mean age of 41 years (range 18 to 75), were 88% male, and were 74% Caucasian. Mean baseline CD4 cell count was 389 cells/mm^3 and mean baseline plasma HIV RNA was 3.9 log10 copies/mL (7,954 copies/mL).

The percent of patients with plasma HIV RNA < 500 copies/mL at 48 weeks was 42%, 62%, and 72% for the VIRACEPT (n=66), EFV (n=65), and VIRACEPT + EFV (n=64) treatment groups, respectively. The 4-drug combination of VIRACEPT + EFV + 2 NRTIs was more effective in suppressing plasma HIV RNA in these patients than either 3-drug regimen.

CONTRAINDICATIONS

VIRACEPT is contraindicated in patients with clinically significant hypersensitivity to any of its components.

Coadministration of VIRACEPT is contraindicated with drugs that are highly dependent on CYP3A for clearance and for which elevated plasma concentrations are associated with serious and/or life-threatening events. These drugs are listed in Table 9.

Table 9 Drugs That Are Contraindicated With VIRACEPT
Drug Class | Drugs Within Class That Are Contraindicated With VIRACEPT
Alpha 1-adrenoreceptor antagonist | Alfuzosin
Antiarrhythmics | Amiodarone, Quinidine
Ergot Derivatives | Dihydroergotamine, Ergonovine, Ergotamine, Methylergonovine
Neuroleptic | Pimozide
PDE5 inhibitors | Sildenafil (REVATIO®) [for treatment of pulmonary arterial hypertension]
Sedative/Hypnotics | Midazolam, Triazolam

WARNINGS

ALERT: Find out about medicines that should not be taken with VIRACEPT. This statement is included on the product's bottle label.

Drug Interactions

(also see PRECAUTIONS)

Nelfinavir is an inhibitor of the CYP3A enzyme. Coadministration of VIRACEPT and drugs primarily metabolized by CYP3A may result in increased plasma concentrations of the other drug that could increase or prolong its therapeutic and adverse effects. Caution should be exercised when inhibitors of CYP3A, including VIRACEPT, are coadministered with drugs that are metabolized by CYP3A and that prolong the QT interval. (See ADVERSE REACTIONS: Post-Marketing Experience.) Nelfinavir is metabolized by CYP3A and CYP2C19. Coadministration of VIRACEPT and drugs that induce CYP3A or CYP2C19 may decrease nelfinavir plasma concentrations and reduce its therapeutic effect. Coadministration of VIRACEPT and drugs that inhibit CYP3A or CYP2C19 may increase nelfinavir plasma concentrations. (Also see PRECAUTIONS: Table 10: Drugs That Should Not Be Coadministered With VIRACEPT, Table 11: Established and Other Potentially Significant Drug Interactions.)

Concomitant use of VIRACEPT with lovastatin or simvastatin is not recommended. Caution should be exercised if HIV protease inhibitors, including VIRACEPT, are used concurrently with other HMG-CoA reductase inhibitors that are also metabolized by the CYP3A pathway (e.g., atorvastatin). (Also see Tables 6 and 7: Drug Interactions). The risk of myopathy including rhabdomyolysis may be increased when protease inhibitors, including VIRACEPT, are used in combination with these drugs.

Particular caution should be used when prescribing sildenafil, or other PDE5 inhibitors, in patients receiving protease inhibitors, including VIRACEPT. Coadministration of these drugs is expected to substantially increase PDE5 inhibitor concentrations and may result in an increase in PDE5 inhibitor-associated adverse events, including hypotension, visual changes, and priapism. (See PRECAUTIONS, Drug Interactions and Information For Patients, and the complete prescribing information for sildenafil and other PDE5 inhibitors.)

Concomitant use of St. John's wort (hypericum perforatum) or St. John's wort-containing products and VIRACEPT is not recommended. Coadministration of St. John's wort with protease inhibitors, including VIRACEPT, is expected to substantially decrease protease inhibitor concentrations and may result in sub-optimal levels of VIRACEPT and lead to loss of virologic response and possible resistance to VIRACEPT or to the class of protease inhibitors.

Patients with Phenylketonuria: VIRACEPT Oral Powder contains 11.2 mg phenylalanine per gram of powder.

Diabetes mellitus/Hyperglycemia

New onset diabetes mellitus, exacerbation of pre-existing diabetes mellitus and hyperglycemia have been reported during post-marketing surveillance in HIV-infected patients receiving protease inhibitor therapy. Some patients required either initiation or dose adjustments of insulin or oral hypoglycemic agents for treatment of these events. In some cases diabetic ketoacidosis has occurred. In those patients who discontinued protease inhibitor therapy, hyperglycemia persisted in some cases. Because these events have been reported voluntarily during clinical practice, estimates of frequency cannot be made and a causal relationship between protease inhibitor therapy and these events has not been established.

PRECAUTIONS

General

Nelfinavir is principally metabolized by the liver. See DOSAGE AND ADMINISTRATION when administering this drug to patients with hepatic impairment.

Resistance/Cross Resistance

HIV cross-resistance between protease inhibitors has been observed. (See MICROBIOLOGY.)

Hemophilia

There have been reports of increased bleeding, including spontaneous skin hematomas and hemarthrosis, in patients with hemophilia type A and B treated with protease inhibitors. In some patients, additional factor VIII was given. In more than half of the reported cases, treatment with protease inhibitors was continued or reintroduced. A causal relationship has not been established.

Fat Redistribution

Redistribution/accumulation of body fat including central obesity, dorsocervical fat enlargement ("buffalo hump"), peripheral wasting, facial wasting, breast enlargement, and "cushingoid appearance" have been observed in patients receiving antiretroviral therapy. The mechanism and long-term consequences of these events are currently unknown. A causal relationship has not been established.

Immune reconstitution syndrome has been reported in patients treated with combination antiretroviral therapy, including VIRACEPT. During the initial phase of combination antiretroviral treatment, patients whose immune system responds may develop an inflammatory response to indolent or residual opportunistic infections (such as Mycobacterium avium infection, cytomegalovirus, Pneumocystis jirovecii pneumonia (PCP), or tuberculosis), which may necessitate further evaluation and treatment.

Information For Patients

A statement to patients and healthcare providers is included on the product's bottle label: ALERT: Find out about medicines that should NOT be taken with VIRACEPT. A Patient Package Insert (PPI) for VIRACEPT is available for patient information.

For optimal absorption, patients should be advised to take VIRACEPT with food (see CLINICAL PHARMACOLOGY: Pharmacokinetics and DOSAGE AND ADMINISTRATION).

Patients should be informed that VIRACEPT is not a cure for HIV infection and that they may continue to acquire illnesses associated with advanced HIV infection, including opportunistic infections.

Patients should be told that there is currently no data demonstrating that VIRACEPT therapy can reduce the risk of transmitting HIV to others through sexual contact or blood contamination.

Patients should be told that sustained decreases in plasma HIV RNA have been associated with a reduced risk of progression to AIDS and death. Patients should be advised to take VIRACEPT and other concomitant antiretroviral therapy every day as prescribed. Patients should not alter the dose or discontinue therapy without consulting with their doctor. If a dose of VIRACEPT is missed, patients should take the dose as soon as possible and then return to their normal schedule. However, if a dose is skipped, the patient should not double the next dose.

Patients should be informed that VIRACEPT Tablets are film-coated and that this film-coating is intended to make the tablets easier to swallow.

The most frequent adverse event associated with VIRACEPT is diarrhea, which can usually be controlled with non-prescription drugs, such as loperamide, which slow gastrointestinal motility.

Patients should be informed that redistribution or accumulation of body fat may occur in patients receiving antiretroviral therapy and that the cause and long-term health effects of these conditions are not known at this time.

VIRACEPT may interact with some drugs; therefore, patients should be advised to report to their doctor the use of any other prescription, non-prescription medication or herbal products, particularly St. John's wort.

Patients receiving oral contraceptives should be instructed that alternate or additional contraceptive measures should be used during therapy with VIRACEPT.

Patients receiving sildenafil, or other PDE5 inhibitors, and nelfinavir should be advised that they may be at an increased risk of PDE5 inhibitor-associated adverse events including hypotension, visual changes, and prolonged penile erection, and should promptly report any symptoms to their doctor.

Drug Interactions

(Also see CONTRAINDICATIONS, WARNINGS, CLINICAL PHARMACOLOGY: Drug Interactions)

Nelfinavir is an inhibitor of CYP3A. Coadministration of VIRACEPT and drugs primarily metabolized by CYP3A (e.g., dihydropyridine calcium channel blockers, HMG-CoA reductase inhibitors, immunosuppressants and PDE5 inhibitors) may result in increased plasma concentrations of the other drug that could increase or prolong both its therapeutic and adverse effects. (See Tables 10 and 11). Nelfinavir is metabolized by CYP3A and CYP2C19. Coadministration of VIRACEPT and drugs that induce CYP3A or CYP2C19, such as rifampin, may decrease nelfinavir plasma concentrations and reduce its therapeutic effect. Coadministration of VIRACEPT and drugs that inhibit CYP3A or CYP2C19 may increase nelfinavir plasma concentrations.

Drug interaction studies reveal no clinically significant drug interactions between nelfinavir and didanosine, lamivudine, stavudine, zidovudine, efavirenz, nevirapine, or ketoconazole and no dose adjustments are needed. In the case of didanosine, it is recommended that didanosine be administered on an empty stomach; therefore, nelfinavir should be administered with food one hour after or more than 2 hours before didanosine.

Based on known metabolic profiles, clinically significant drug interactions are not expected between VIRACEPT and dapsone, trimethoprim/sulfamethoxazole, or itraconazole.

Table 10 Drugs That Should Not Be Coadministered With VIRACEPT
Drug Class: Drug Name | Clinical Comment
Alpha 1-adrenoreceptor antagonist: alfuzosin | Potentially increased alfuzosin concentrations can result in hypotension.
Antiarrhythmics: amiodarone, quinidine | CONTRAINDICATED due to potential for serious and/or life threatening reactions such as cardiac arrhythmias.
Antimycobacterial: rifampin | May lead to loss of virologic response and possible resistance to VIRACEPT or other coadministered antiretroviral agents.
Ergot Derivatives: dihydroergotamine, ergonovine, ergotamine, methylergonovine | CONTRAINDICATED due to potential for serious and/or life threatening reactions such as acute ergot toxicity characterized by peripheral vasospasm and ischemia of the extremities and other tissues.
Herbal Products: St. John's wort (hypericum perforatum) | May lead to loss of virologic response and possible resistance to VIRACEPT or other coadministered antiretroviral agents.
HMG-CoA Reductase Inhibitors: lovastatin, simvastatin | Potential for serious reactions such as risk of myopathy including rhabdomyolysis.
Neuroleptic: pimozide | CONTRAINDICATED due to potential for serious and/or life threatening reactions such as cardiac arrhythmias.
PDE5 inhibitor: sildenafil (REVATIO) [for treatment of pulmonary arterial hypertension] | A safe and effective dose has not been established when used with VIRACEPT. There is increased potential for sildenafil-associated adverse events (which include visual disturbances, hypotension, prolonged erection, and syncope).
Proton Pump Inhibitors | Omeprazole decreases the plasma concentrations of nelfinavir. Concomitant use of proton pump inhibitors and VIRACEPT may lead to a loss of virologic response and development of resistance.
Sedative/Hypnotics: midazolam, triazolam | CONTRAINDICATED due to potential for serious and/or life threatening reactions such as prolonged or increased sedation or respiratory depression.

Table 11 Established and Other Potentially Significant Drug Interactions: Alteration in Dose or Regimen May Be Recommended Based on Drug Interaction Studies (see CLINICAL PHARMACOLOGY, for Magnitude of Interaction, Tables 6 and 7)
Concomitant Drug Class: Drug Name | Effect on Concentration | Clinical Comment
HIV-Antiviral Agents
Non-nucleoside Reverse Transcriptase Inhibitors: |  | Appropriate doses for these combinations, with respect to safety and efficacy, have not been established.
delavirdine | ↑ nelfinavir ↓ delavirdine | Appropriate doses for these combinations, with respect to safety and efficacy, have not been established.
nevirapine | ↓ nelfinavir (Cmin) | Appropriate doses for these combinations, with respect to safety and efficacy, have not been established.
Nucleoside Reverse Transcriptase Inhibitor: didanosine |  | It is recommended that didanosine be administered on an empty stomach; therefore, didanosine should be given one hour before or two hours after VIRACEPT (given with food).
Protease Inhibitors: |  | Appropriate doses for these combinations, with respect to safety and efficacy, have not been established.
indinavir | ↑ nelfinavir ↑ indinavir | Appropriate doses for these combinations, with respect to safety and efficacy, have not been established.
ritonavir | ↑ nelfinavir | Appropriate doses for these combinations, with respect to safety and efficacy, have not been established.
saquinavir | ↑ saquinavir | Appropriate doses for these combinations, with respect to safety and efficacy, have not been established.
Other Agents
Anti-coagulant: warfarin | warfarin | Coadministration of warfarin and VIRACEPT may affect concentrations of warfarin. It is recommended that the INR (international normalized ratio) be monitored carefully during treatment with VIRACEPT, especially when commencing therapy.
Anti-convulsants: |  | May decrease nelfinavir plasma concentrations. VIRACEPT may not be effective due to decreased nelfinavir plasma concentrations in patients taking these agents concomitantly.
carbamazepine phenobarbital | ↓ nelfinavir | May decrease nelfinavir plasma concentrations. VIRACEPT may not be effective due to decreased nelfinavir plasma concentrations in patients taking these agents concomitantly.
Anti-convulsant: |  | Phenytoin plasma/serum concentrations should be monitored; phenytoin dose may require adjustment to compensate for altered phenytoin concentration.
phenytoin | ↓ phenytoin | Phenytoin plasma/serum concentrations should be monitored; phenytoin dose may require adjustment to compensate for altered phenytoin concentration.
Anti-depressant: trazodone | ↑ trazodone | Concomitant use of trazodone and VIRACEPT may increase plasma concentrations of trazodone. Adverse events of nausea, dizziness, hypotension and syncope have been observed following coadministration of trazodone and ritonavir. If trazodone is used with a CYP3A4 inhibitor such as VIRACEPT, the combination should be used with caution and a lower dose of trazodone should be considered.
Anti-gout colchicine | ↑ colchicine | Treatment of gout flares– coadministration of colchicine in patients on VIRACEPT:; 0.6 mg (1 tablet) × 1 dose, followed by 0.3 mg (half tablet) 1 hour later. Dose to be repeated no earlier than 3 days.; Prophylaxis of gout-flares– coadministration of colchicine in patients on VIRACEPT: If the original colchicine regimen was 0.6 mg twice a day, the regimen should be adjusted to 0.3 mg once a day. If the original colchicine regimen was 0.6 mg once a day, the regimen should be adjusted to 0.3 mg once every other day.; Treatment of familial Mediterranean fever (FMF)– coadministration of colchicine in patients on VIRACEPT:; Maximum daily dose of 0.6 mg (may be given as 0.3 mg twice a day). Patients with renal or hepatic impairment should not be given colchicine with VIRACEPT.
Anti-Mycobacterial: |  | It is recommended that the dose of rifabutin be reduced to one-half the usual dose when administered with VIRACEPT; 1250 mg BID is the preferred dose of VIRACEPT when coadministered with rifabutin.
rifabutin | ↑ rifabutin ↓ nelfinavir (750 mg TID) ↔ nelfinavir (1250 mg BID) | It is recommended that the dose of rifabutin be reduced to one-half the usual dose when administered with VIRACEPT; 1250 mg BID is the preferred dose of VIRACEPT when coadministered with rifabutin.
Endothelin receptor antagonists: bosentan | ↑ bosentan | Coadministration of bosentan in patients on VIRACEPT or coadministration of VIRACEPT in patients on bosentan:; Start at or adjust bosentan to 62.5 mg once daily or every other day based upon individual tolerability.
HMG-CoA Reductase Inhibitor: |  | Use lowest possible dose of atorvastatin or rosuvastatin with careful monitoring, or consider other HMG-CoA reductase inhibitors such as pravastatin or fluvastatin in combination with VIRACEPT.
atorvastatin | ↑ atorvastatin | Use lowest possible dose of atorvastatin or rosuvastatin with careful monitoring, or consider other HMG-CoA reductase inhibitors such as pravastatin or fluvastatin in combination with VIRACEPT.
rosuvastatin | ↑ rosuvastatin | Use lowest possible dose of atorvastatin or rosuvastatin with careful monitoring, or consider other HMG-CoA reductase inhibitors such as pravastatin or fluvastatin in combination with VIRACEPT.
Immuno-suppressants: |  | Plasma concentrations may be increased by VIRACEPT.
cyclosporine tacrolimus sirolimus | ↑ immuno-suppressants | Plasma concentrations may be increased by VIRACEPT.
Inhaled beta agonist: salmeterol | ↑ salmeterol | Concurrent administration of salmeterol with VIRACEPT is not recommended. The combination may result in increased risk of cardiovascular adverse events associated with salmeterol, including QT prolongation, palpitations and sinus tachycardia.
Inhaled/nasal steroid: Fluticasone | ↑ fluticasone | Concomitant use of fluticasone propionate and VIRACEPT may increase plasma concentrations of fluticasone propionate. Use with caution. Consider alternatives to fluticasone propionate, particularly for long-term use.
Macrolide Antibiotic: azithromycin | ↑ azithromycin | Dose adjustment of azithromycin is not recommended, but close monitoring for known side effects such as liver enzyme abnormalities and hearing impairment is warranted.
Narcotic Analgesic: |  | Dosage of methadone may need to be increased when coadministered with VIRACEPT.
methadone | ↓ methadone | Dosage of methadone may need to be increased when coadministered with VIRACEPT.
Oral Contraceptive: |  | Alternative or additional contraceptive measures should be used when oral contraceptives and VIRACEPT are coadministered.
ethinyl estradiol | ↓ ethinyl estradiol | Alternative or additional contraceptive measures should be used when oral contraceptives and VIRACEPT are coadministered.
PDE5 Inhibitors: sildenafil vardenafil tadalafil | ↑ PDE5 Inhibitors | Concomitant use of PDE5 inhibitors and VIRACEPT should be undertaken with caution.; May result in an increase in PDE5 inhibitor-associated adverse events, including hypotension, syncope, visual disturbances, and priapism.; Use of PDE-5 inhibitors for pulmonary arterial hypertension (PAH):; - Use of sildenafil (REVATIO) is contraindicated when used for the treatment of pulmonary arterial hypertension (PAH) [see Contraindications]. - The following dose adjustments are recommended for use of tadalafil (ADCIRCA™) with VIRACEPT:; Coadministration of ADCIRCA in patients on VIRACEPT or coadministration of VIRACEPT in patients on ADCIRCA:; Start at or adjust ADCIRCA to 20 mg once daily. Increase to 40 mg once daily based upon individual tolerability.; Use of PDE5 inhibitors for erectile dysfunction:; Sildenafil at a single dose not exceeding 25 mg in 48 hours, vardenafil at a single dose not exceeding 2.5 mg in 24 hours, or tadalafil at a single dose not exceeding 10 mg dose in 72 hours, is recommended. Use with increased monitoring for adverse events.

Carcinogenesis, Mutagenesis, Impairment of Fertility

Carcinogenicity studies in mice and rats were conducted with nelfinavir at oral doses up to 1000 mg/kg/day. No evidence of a tumorigenic effect was noted in mice at systemic exposures (Cmax) up to 9-fold those measured in humans at the recommended therapeutic dose (750 mg TID or 1250 mg BID). In rats, thyroid follicular cell adenomas and carcinomas were increased in males at 300 mg/kg/day and higher and in females at 1000 mg/kg/day. Systemic exposures (Cmax) at 300 and 1000 mg/kg/day were 1- to 3-fold, respectively, those measured in humans at the recommended therapeutic dose. Repeated administration of nelfinavir to rats produced effects consistent with hepatic microsomal enzyme induction and increased thyroid hormone deposition; these effects predispose rats, but not humans, to thyroid follicular cell neoplasms. Nelfinavir showed no evidence of mutagenic or clastogenic activity in a battery of in vitro and in vivo genetic toxicology assays. These studies included bacterial mutation assays in S. typhimurium and E. coli, a mouse lymphoma tyrosine kinase assay, a chromosomal aberration assay in human lymphocytes, and an in vivo mouse bone marrow micronucleus assay.

Nelfinavir produced no effects on either male or female mating and fertility or embryo survival in rats at systemic exposures comparable to the human therapeutic exposure.

Pregnancy - Pregnancy Category B

There were no effects on fetal development or maternal toxicity when nelfinavir was administered to pregnant rats at systemic exposures (AUC) comparable to human exposure. Administration of nelfinavir to pregnant rabbits resulted in no fetal development effects up to a dose at which a slight decrease in maternal body weight was observed; however, even at the highest dose evaluated, systemic exposure in rabbits was significantly lower than human exposure. Additional studies in rats indicated that exposure to nelfinavir in females from mid-pregnancy through lactation had no effect on the survival, growth, and development of the offspring to weaning. Subsequent reproductive performance of these offspring was also not affected by maternal exposure to nelfinavir. However, there are no adequate and well-controlled studies in pregnant women taking VIRACEPT. Because animal reproduction studies are not always predictive of human response, VIRACEPT should be used during pregnancy only if clearly needed.

Antiretroviral Pregnancy Registry: (APR)

To monitor maternal-fetal outcomes of pregnant women exposed to VIRACEPT and other antiretroviral agents, an Antiretroviral Pregnancy Registry has been established. Physicians are encouraged to register patients by calling (800) 258-4263.

Nursing Mothers

The Centers for Disease Control and Prevention recommends that HIV-infected mothers not breast-feed their infants to avoid risking postnatal transmission of HIV. Studies in lactating rats have demonstrated that nelfinavir is excreted in milk. Because of both the potential for HIV transmission and the potential for serious adverse reactions in nursing infants, mothers should be instructed not to breast-feed if they are receiving VIRACEPT.

Pediatric Use

The safety and effectiveness of VIRACEPT have been established in patients from 2 to 13 years of age. The use of VIRACEPT in these age groups is supported by evidence from adequate and well-controlled studies of VIRACEPT in adults and pharmacokinetic studies and studies supporting activity in pediatric patients. In patients less than 2 years of age, VIRACEPT was found to be safe at the doses studied, but a reliably effective dose could not be established (see CLINICAL PHARMACOLOGY: Special Populations, ADVERSE REACTIONS: Pediatric Population, and DOSAGE AND ADMINISTRATION: Pediatric Patients).

The following issues should be considered when initiating VIRACEPT in pediatric patients:

- In pediatric patients ≥ 2 years of age receiving VIRACEPT as part of triple combination antiretroviral therapy in randomized studies, the proportion of patients achieving a HIV RNA level <400 copies/mL through 48 weeks ranged from 26% to 42%.
- Response rates in children <2 years of age appeared to be poorer than those in patients ≥ 2 years of age in some studies.
- Highly variable drug exposure remains a significant problem in the use of VIRACEPT in pediatric patients. Unpredictable drug exposure may be exacerbated in pediatric patients because of increased clearance compared to adults and difficulties with compliance and adequate food intake with dosing. Pharmacokinetic results from the pediatric studies are reported in Table 5 (see CLINICAL PHARMACOLOGY, Special Populations).

Study 556 was a randomized, double-blind, placebo-controlled trial with VIRACEPT or placebo coadministered with ZDV and ddI in 141 HIV-positive children who had received minimal antiretroviral therapy. The mean age of the children was 3.9 years. Ninety four (67%) children were between 2–12 years, and 47 (33%) were < 2 years of age. The mean baseline HIV RNA value was 5.0 log for all patients and the mean CD4 cell count was 886 cells/mm^3 for all patients. The efficacy of VIRACEPT measured by HIV RNA <400 at 48 weeks in children ≥ 2 years of age was 26% compared to 2% of placebo patients (p=0.0008). In the children < 2 years of age, only 1 of 27 and 2 of 20 maintained an undetectable HIV RNA level at 48 weeks for placebo and VIRACEPT patients, respectively.

PACTG 377 was an open-label study that randomized 181 HIV treatment-experienced pediatric patients to receive: d4T+NVP+RTV, d4T+3TC+NFV, or d4T+3TC+NVP+NFV with NFV given on a TID schedule. The median age was 5.9 years and 46% were male. At baseline the median HIV RNA was 4.4 log and median CD4 cell count was 690 cells/mm^3. Substudy PACTG 725 evaluated d4T+3TC+NFV with NFV given on a BID schedule. The proportion of patients with detectable viral load at baseline achieving HIV RNA <400 copies/mL at 48 weeks was: 41% for d4T+NVP+RTV, 42% for d4T+3TC+NFV, 30% for d4T+NVP+NFV, and 52% for d4T+3TC+NVP+NFV. No significant clinical differences were identified between patients receiving VIRACEPT in BID or TID schedules.

VIRACEPT has been evaluated in 2 studies of young infants. The PENTA 7 study was an open-label study to evaluate the toxicity, tolerability, pharmacokinetics, and activity of NFV+d4T+ddI in 20 HIV-infected infants less than 12 weeks of age. PACTG 353 evaluated the pharmacokinetics and safety of VIRACEPT in infants born to HIV-infected women receiving NFV as part of combination therapy during pregnancy.

Geriatric Use

Clinical studies of VIRACEPT did not include sufficient numbers of subjects aged 65 and over to determine whether they respond differently from younger subjects.

ADVERSE REACTIONS

The safety of VIRACEPT was studied in over 5000 patients who received drug either alone or in combination with nucleoside analogues. The majority of adverse events were of mild intensity. The most frequently reported adverse event among patients receiving VIRACEPT was diarrhea, which was generally of mild to moderate intensity.

Drug-related clinical adverse experiences of moderate or severe intensity in ≥ 2% of patients treated with VIRACEPT coadministered with d4T and 3TC (Study 542) for up to 48 weeks or with ZDV plus 3TC (Study 511) for up to 24 weeks are presented in Table 12.

Table 12 Percentage of Patients with Treatment-Emergent [Includes those adverse events at least possibly related to study drug or of unknown relationship and excludes concurrent HIV conditions] Adverse Events of Moderate or Severe Intensity Reported in ≥ 2% of Patients
 | Study 511 24 weeks |  |  | Study 542 48 weeks
Adverse Events | Placebo + ZDV/3TC (n=101) | 500 mg TID VIRACEPT + ZDV/3TC (n=97) | 750 mg TID VIRACEPT + ZDV/3TC (n=100) | 1250 mg BID VIRACEPT + d4T/3TC (n=344) | 750 mg TID VIRACEPT + d4T/3TC (n=210)
Digestive System
Diarrhea | 3% | 14% | 20% | 20% | 15%
Nausea | 4% | 3% | 7% | 3% | 3%
Flatulence | 0 | 5% | 2% | 1% | 1%
Skin/Appendages
Rash | 1% | 1% | 3% | 2% | 1%

Adverse events occurring in less than 2% of patients receiving VIRACEPT in all phase II/III clinical trials and considered at least possibly related or of unknown relationship to treatment and of at least moderate severity are listed below.

Body as a Whole: abdominal pain, accidental injury, allergic reaction, asthenia, back pain, fever, headache, malaise, pain, and redistribution/accumulation of body fat (see PRECAUTIONS, Fat Redistribution).

Digestive System: anorexia, dyspepsia, epigastric pain, gastrointestinal bleeding, hepatitis, mouth ulceration, pancreatitis, and vomiting.

Hemic/Lymphatic System: anemia, leukopenia, and thrombocytopenia.

Metabolic/Nutritional System: increases in alkaline phosphatase, amylase, creatine phosphokinase, lactic dehydrogenase, SGOT, SGPT, and gamma glutamyl transpeptidase; hyperlipemia, hyperuricemia, hyperglycemia, hypoglycemia, dehydration, and liver function tests abnormal.

Musculoskeletal System: arthralgia, arthritis, cramps, myalgia, myasthenia, and myopathy.

Nervous System: anxiety, depression, dizziness, emotional lability, hyperkinesia, insomnia, migraine, paresthesia, seizures, sleep disorder, somnolence, and suicide ideation.

Respiratory System: dyspnea, pharyngitis, rhinitis, and sinusitis.

Skin/Appendages: dermatitis, folliculitis, fungal dermatitis, maculopapular rash, pruritus, sweating, and urticaria.

Special Senses: acute iritis and eye disorder.

Urogenital System: kidney calculus, sexual dysfunction, and urine abnormality.

Post-Marketing Experience

The following additional adverse experiences have been reported from postmarketing surveillance as at least possibly related or of unknown relationship to VIRACEPT:

Body as a Whole: hypersensitivity reactions (including bronchospasm, moderate to severe rash, fever, and edema).

Cardiovascular System: QTc prolongation, torsades de pointes.

Digestive System: jaundice.

Metabolic/Nutritional System: bilirubinemia, metabolic acidosis.

Laboratory Abnormalities

The percentage of patients with marked laboratory abnormalities in Studies 542 and 511 are presented in Table 13. Marked laboratory abnormalities are defined as a Grade 3 or 4 abnormality in a patient with a normal baseline value, or a Grade 4 abnormality in a patient with a Grade 1 abnormality at baseline.

Table 13 Percentage of Patients by Treatment Group With Marked Laboratory Abnormalities [Marked laboratory abnormalities are defined as a shift from Grade 0 at baseline to at least Grade 3 or from Grade 1 to Grade 4] in > 2% of Patients
 | Study 511 |  |  | Study 542
 | Placebo + ZDV/3TC (n=101) | 500 mg TID VIRACEPT + ZDV/3TC (n=97) | 750 mg TID VIRACEPT + ZDV/3TC (n=100) | 1250 mg BID VIRACEPT + d4T/3TC (n=344) | 750 mg TID VIRACEPT + d4T/3TC (n=210)
Hematology
Hemoglobin | 6% | 3% | 2% | 0 | 0
Neutrophils | 4% | 3% | 5% | 2% | 1%
Lymphocytes | 1% | 6% | 1% | 1% | 0
Chemistry
ALT (SGPT) | 6% | 1% | 1% | 2% | 1%
AST (SGOT) | 4% | 1% | 0 | 2% | 1%
Creatine Kinase | 7% | 2% | 2% | NA | NA

Pediatric Population

VIRACEPT has been studied in approximately 400 pediatric patients in clinical trials from birth to 13 years of age. The adverse event profile seen during pediatric clinical trials was similar to that for adults.

The most commonly reported drug-related, treatment-emergent adverse events reported in the pediatric studies included: diarrhea, leukopenia/neutropenia, rash, anorexia, and abdominal pain. Diarrhea, regardless of assigned relationship to study drug, was reported in 39% to 47% of pediatric patients receiving VIRACEPT in 2 of the larger treatment trials. Leukopenia/neutropenia was the laboratory abnormality most commonly reported as a significant event across the pediatric studies.

OVERDOSAGE

Human experience of acute overdose with VIRACEPT is limited. There is no specific antidote for overdose with VIRACEPT. If indicated, elimination of unabsorbed drug should be achieved by emesis or gastric lavage. Administration of activated charcoal may also be used to aid removal of unabsorbed drug. Since nelfinavir is highly protein bound, dialysis is unlikely to significantly remove drug from blood.

DOSAGE AND ADMINISTRATION

Adults

The recommended dose is 1250 mg (five 250 mg tablets or two 625 mg tablets) twice daily or 750 mg (three 250 mg tablets) three times daily. VIRACEPT should be taken with a meal. Patients unable to swallow the 250 or 625 mg tablets may dissolve the tablets in a small amount of water. Once dissolved, patients should mix the cloudy liquid well, and consume it immediately. The glass should be rinsed with water and the rinse swallowed to ensure the entire dose is consumed.

Pediatric Patients (2–13 years)

In children 2 years of age and older, the recommended oral dose of VIRACEPT Oral Powder or 250 mg tablets is 45 to 55 mg/kg twice daily or 25 to 35 mg/kg three times daily. All doses should be taken with a meal. Doses higher than the adult maximum dose of 2500 mg per day have not been studied in children. For children unable to take tablets, VIRACEPT Oral Powder may be administered. The oral powder may be mixed with a small amount of water, milk, formula, soy formula, soy milk, or dietary supplements; once mixed, the entire contents must be consumed in order to obtain the full dose. If the mixture is not consumed immediately, it must be stored under refrigeration, but storage must not exceed 6 hours. Acidic food or juice (e.g., orange juice, apple juice, or apple sauce) are not recommended to be used in combination with VIRACEPT, because the combination may result in a bitter taste. VIRACEPT Oral Powder should not be reconstituted with water in its original container.

The healthcare provider should assess appropriate formulation and dosage for each patient. Crushed 250 mg tablets can be used in lieu of powder. Tables 14 and 15 provide dosing guidelines for VIRACEPT tablets and powder based on age and body weight.

Table 14 Dosing Table for Children ≥ 2 years of age (tablets)
Body weight |  | Twice daily (BID) 45 – 55 mg/kg ≥2 years | Three times daily (TID) 25 – 35 mg/kg ≥2 years
Kg. | Lbs. | # of tablets (250 mg) | # of tablets (250 mg)
10 – 12 | 22 –26.4 | 2 | 1
13 – 18 | 28.6 – 39.6 | 3 | 2
19 – 20 | 41.8 – 44 | 4 | 2
≥21 | ≥46.2 | 4 – 5 [For BID dosing, the maximum dose per day is 5 tablets BID] | 3 [For TID dosing, the maximum dose per day is 3 tablets TID]

Table 15 Dosing Table for Children ≥ 2 years of age (powder)
Body weight |  | Twice daily (BID) 45 – 55 mg/kg |  | Three times daily (TID) 25 – 35 mg/kg
Kg. | Lbs. | Scoops of powder (50 mg/1 g) | Teaspoons [If a teaspoon is used to measure VIRACEPT oral powder, 1 level teaspoon contains 200 mg of VIRACEPT (4 level scoops equals 1 level teaspoon)] of powder | Scoops of powder (50 mg/1 g) | Teaspoons of powder
9.0 to < 10.5 | 20 to < 23 | 10 | 2½ | 6 | 1½
10.5 to < 12 | 23 to < 26.5 | 11 | 2¾ | 7 | 1¾
12 to < 14 | 26.5 to < 31 | 13 | 3¼ | 8 | 2
14 to < 16 | 31 to < 35 | 15 | 3¾ | 9 | 2¼
16 to < 18 | 35 to < 39.5 | Not recommended [Use VIRACEPT 250 mg tablet] | Not recommended | 10 | 2½
18 to < 23 | 39.5 to < 50.5 | Not recommended | Not recommended | 12 | 3
≥23 | ≥50.5 | Not recommended | Not recommended | 15 | 3¾

Hepatic Impairment

Viracept can be used in patients with mild hepatic impairment without any dose adjustment. VIRACEPT should not be used in patients with either moderate or severe hepatic impairment (see CLINICAL PHARMACOLOGY: Special Populations).

HOW SUPPLIED

VIRACEPT (nelfinavir mesylate) 250 mg: Light blue, capsule-shaped tablets with a clear film coating engraved with "VIRACEPT" on one side and "250 mg" on the other.

Bottles of 300, 250 mg tablets………………………………...NDC 63010-010-30

VIRACEPT (nelfinavir mesylate) 625 mg: White oval tablet with a clear film coating engraved with "V" on one side and "625" on the other.

Bottles of 120, 625 mg tablets………………………………...NDC 63010-027-70

VIRACEPT (nelfinavir mesylate) Oral Powder is available as a 50 mg/g off-white powder containing 50 mg (as nelfinavir free base) in each level scoopful (1 gram).

Multiple use bottles of 144 grams of powder with scoop …….NDC 63010-011-90

STORAGE AND HANDLING

Viracept tablets and oral powder should be stored at 15° to 30°C (59° TO 86°F).

Keep container tightly closed. Dispense in original container.

VIRACEPT and Agouron are registered trademarks of Agouron Pharmaceuticals, Inc.

REVATIO is a registered trademark of Pfizer, Inc.

ADCIRCA is a trademark of Eli Lilly and Company

AGOURON PHARMACEUTICALS, INC.
La Jolla, CA 92037, USA

LAB-0174-20.0
February 2011

VIRACEPT
Patient Prescribing Information

VIRACEPT® (nelfinavir mesylate) TABLETS and ORAL POWDER

ALERT: Find out about medicines that should NOT be taken with VIRACEPT. Please also read the section "MEDICINES YOU SHOULD NOT TAKE WITH VIRACEPT".

Patient Information

VIRACEPT® (VI-ra-cept)

Generic Name: nelfinavir (nel-FIN-na-veer) mesylate

Please read this information carefully before taking VIRACEPT. Also, please read this leaflet each time you renew the prescription, in case anything has changed. This is a summary and not a replacement for a careful discussion with your healthcare provider. You and your healthcare provider should discuss VIRACEPT when you start taking this medication and at regular checkups. You should remain under a healthcare provider's care when taking VIRACEPT and should not change or stop treatment without first talking with your healthcare provider.

What is VIRACEPT and how does it work?

VIRACEPT is a type of medicine called an HIV (human immunodeficiency virus) protease (PRO-tee-ase) inhibitor. VIRACEPT is always used in combination with other antiretroviral drugs in the treatment of people with HIV infection. VIRACEPT is for adults and for children 2 years of age and older.

Infection with HIV leads to the destruction of CD4 (T) cells, which are important to the immune system. After a large number of CD4 (T) cells have been destroyed, the infected person develops acquired immune deficiency syndrome (AIDS).

VIRACEPT works by blocking HIV protease (a protein-cutting enzyme), which is required for HIV to multiply. VIRACEPT has been shown to significantly reduce the amount of HIV in the blood. Although VIRACEPT is not a cure for HIV or AIDS, VIRACEPT can help reduce your risk for death and illness associated with HIV. Patients who took VIRACEPT also had significant increases in the number of CD4 (T) cells.

Does VIRACEPT cure HIV or AIDS?

VIRACEPT is not a cure for HIV infection or AIDS. People taking VIRACEPT may still develop opportunistic infections or other conditions associated with HIV infection. Some of these conditions are pneumonia, herpes virus infections, Mycobacterium avium complex (MAC) infections, and Kaposi's sarcoma.

Does VIRACEPT reduce the risk of passing HIV to others?

VIRACEPT does not reduce the risk of transmitting HIV to others through sexual contact or blood contamination. Continue to practice safe sex and do not use or share dirty needles.

How should I take VIRACEPT?

- You should stay under a healthcare provider's care when taking VIRACEPT. Do not change your treatment or stop treatment without first talking with your healthcare provider.
- You must take VIRACEPT every day exactly as your healthcare provider prescribed it. Follow the directions from your healthcare provider, exactly as written on the label.
- Dosing in adults (including children 14 years of age and older): The recommended adult dose of VIRACEPT is 1250 mg (five 250 mg tablets or two 625 mg tablets) taken two times a day or 750 mg (three 250 mg tablets) taken three times a day. Each dose should always be taken with a meal to help achieve higher VIRACEPT levels. VIRACEPT Tablets are film-coated to help make the tablets easier to swallow.
- Dosing in children 2 years of age and older: The VIRACEPT dose in children depends on their weight. The recommended oral dose of VIRACEPT oral powder or 250 mg tablets is 45 to 55 mg/kg twice daily or 25 to 35 mg/kg three times daily. All doses should be taken with a meal. Children who cannot swallow tablets may take VIRACEPT Oral Powder or crushed tablets.
- If you or your child is unable to swallow the tablets, dissolve the tablets in a small amount of water. Once dissolved, mix the cloudy liquid well, and consume immediately. The glass should be rinsed with water and the rinse swallowed to ensure the entire dose is consumed.
- Do not change your dose or stop taking VIRACEPT without first consulting with your healthcare provider.
- When your VIRACEPT supply starts to run low, get in touch with your healthcare provider or pharmacy. This is very important because the amount of virus in your blood may increase if the medicine is stopped for even a short time. The virus may develop resistance to antiretroviral medications, including VIRACEPT, but there are other antiretroviral treatment options. Talk to your healthcare provider about how to optimize your long-term treatment.
- Be sure to set up a schedule and follow it carefully.
- Only take medicine that has been prescribed specifically for you. Do not give VIRACEPT to others or take medicine prescribed for someone else.

How should VIRACEPT Oral Powder be prepared?

- The oral powder may be mixed with a small amount of water, milk, formula, soy formula, soy milk, dietary supplements, or dairy foods such as pudding or ice cream. Once mixed, the entire amount must be taken to obtain the full dose. If the mixture is not consumed immediately, it must be stored under refrigeration, but storage must not exceed 6 hours. Do not heat the mixed dose once it has been prepared.
- Do not mix the powder with any acidic food or juice, such as orange or grapefruit juice, apple juice, or apple sauce, because this may create a bitter taste.
- Do not add water to bottles of oral powder.
- VIRACEPT powder is supplied with a scoop for measuring. For help in determining the exact dose of powder for your child, please ask your doctor, nurse, pharmacist, or other healthcare provider.

What should I do if I miss a dose?

If you forget to take a dose of VIRACEPT, take it as soon as possible. However, if you skip the dose entirely, do not double the next dose. If you forget a lot of doses, talk to your healthcare provider about how you should continue taking your medicine.

What happens if I take too much VIRACEPT?

If you suspect that you took more than the prescribed dose of this medicine, contact your local poison control center or emergency room immediately.

Who should not take VIRACEPT?

Together with your healthcare provider, you need to decide whether VIRACEPT is appropriate for you.

- Do not take VIRACEPT if you are taking certain medicines. These could cause serious side effects that could cause death. Before you take VIRACEPT, you must tell your healthcare provider about all medicines you are taking or are planning to take. These include prescription and non-prescription medicines and herbal supplements.

For more information about medicines you should not take with VIRACEPT, please read the section titled "MEDICINES YOU SHOULD NOT TAKE WITH VIRACEPT."

- Do not take VIRACEPT if you have an allergy to VIRACEPT. Also tell your healthcare provider if you have any known allergies to other medicines, foods, preservatives, or dyes.
- Tell your healthcare provider if you are pregnant or plan to become pregnant. The effects of VIRACEPT on pregnant women or their unborn babies are not known.
- If you are breast-feeding, it is very important that you speak with your healthcare provider about the best way to feed your baby. If your baby does not already have HIV, there is a chance that it can be transmitted through breast-feeding. The Centers for Disease Control and Prevention recommends that women with HIV do not breast-feed.
- Talk with your healthcare provider if you have liver or kidney disease. VIRACEPT has not been extensively studied in people with liver or kidney disease. VIRACEPT can be used in patients with mild liver disease without any dose adjustment. VIRACEPT should not be used in patients with either moderate or severe liver disease.
- Certain medical problems may affect the use of VIRACEPT. Be sure to tell your healthcare provider of any other medical problems you may have.

Can VIRACEPT be taken with other medications?

VIRACEPT may interact with other drugs, including those you take without a prescription. You must tell your healthcare provider about all medicines you are taking or planning to take before you take VIRACEPT. It is a good idea to keep a complete list of all the medicines that you take, including non-prescription medicines, herbal remedies and supplements and street drugs. Update this list when medicines are added or stopped. Give copies of this list to all of your healthcare providers every time you visit or fill a prescription.

MEDICINES YOU SHOULD NOT TAKE WITH VIRACEPT:

Do not take the following drugs because they can cause serious problems or death if taken with VIRACEPT:

- Cordarone® (amiodarone) (for irregular heartbeat)
- Orap® (pimozide) (for seizures)
- Quinidine (for irregular heartbeat), also known as Quinaglute®, Cardioquin®, Quinidex®, and others
- D.H.E. 45® Injection, Ergomar, Migranal®, Wigraine® and Cafergot® (for migraine headaches) and Methergine® (for bleeding after childbirth)
- Halcion® (triazolam) (for sleep problem)
- Versed® (midazolam) (sedative hypnotic)
- Revatio® (sildenafil) (for treatment of pulmonary arterial hypertension)
- Alfuzosin (for treatment of benign prostate enlargement)

Do not take the following medicines when you take VIRACEPT. They may reduce the levels of VIRACEPT in the blood and make it less effective. Talk with your healthcare provider if you are currently taking these medicines because other medicines may have to be given to take their place:

- Prilosec® (omeprazole) (for stomach acid reduction)
- Rifampin (also known as Rimactane®, Rifadin®, Rifater®, or Rifamate®) (for tuberculosis)
- Phenobarbital (for seizures)
- Tegretol® (carbamazepine) (for seizures)

Do not take VIRACEPT with St. John's wort (hypericum perforatum), an herbal product sold as a dietary supplement, or products containing St. John's wort. Talk with your healthcare provider if you are taking or planning to take St. John's wort. Taking St. John's wort may decrease VIRACEPT levels and lead to increased viral load and possible resistance to VIRACEPT.

Do not take VIRACEPT with cholesterol-lowering medicines Mevacor® (lovastatin) or Zocor® (simvastatin) because of possible serious reactions.

Do not take VIRACEPT with Serevent® (salmeterol) because of possible serious reactions.

Talk to your healthcare provider before you start taking any new prescription or non-prescription medicines or herbal supplements with VIRACEPT.

Medicines that require dose adjustments:

It is possible that your healthcare provider may need to increase or decrease the dose of other medicines when you are also taking VIRACEPT.

There is also an increased risk of drug interactions between VIRACEPT and Lipitor® (atorvastatin), Crestor® (rosuvastatin), Pravachol® (pravastatin) and Lescol® (fluvastatin); talk to your healthcare provider before you take any of these cholesterol-reducing medicines with VIRACEPT.

Before you take PDE5 Inhibitors, such as Viagra® (sildenafil), Levitra® (vardenafil) or Cialis® (tadalafil) with VIRACEPT, talk to your healthcare provider about possible drug interactions and side effects. If you take these types of drugs and VIRACEPT together, you may be at increased risk of side effects of these drugs such as low blood pressure, visual changes, and penile erection lasting more than 4 hours. If an erection lasts longer than 4 hours, you should seek immediate medical assistance to avoid permanent damage to your penis. Your healthcare provider can explain these symptoms to you.

Before you take Adcirca™ (tadalafil) with VIRACEPT, talk to your healthcare provider since VIRACEPT may increase the amount of tadalafil in your blood.

Before you take Tracleer® (bosentan) with VIRACEPT, talk to your healthcare provider since VIRACEPT may increase the amount of bosentan in your blood.

Before you take colchicine with VIRACEPT, talk to your healthcare provider since VIRACEPT may increase the amount of colchicine in your blood.

Before you take warfarin (Coumadin®) with VIRACEPT, talk to your healthcare provider since VIRACEPT may affect the amount of warfarin in your blood.

- If you are taking both didanosine (Videx®) and VIRACEPT:
  You should take VIRACEPT with food one hour after or more than two hours before you take Videx buffered tablets.
- If you are taking oral contraceptives ("the pill") to prevent pregnancy, you should use an additional or different type of contraception since VIRACEPT may reduce the effectiveness of oral contraceptives.
- Non-nucleoside reverse transcriptase inhibitors (NNRTIs): RESCRIPTOR® (delavirdine) may increase the amount of VIRACEPT in your blood and VIRACEPT may lower the amount of RESCRIPTOR in your blood.
- Protease Inhibitors (PIs): VIRACEPT may increase the amount of Crixivan® (indinavir), Norvir® (ritonavir), and Invirase® or Fortovase® (saquinavir) in your blood. As a result, your healthcare provider may choose to lower the dose of VIRACEPT or one of these other medicines or monitor certain lab tests if VIRACEPT is taken in combination with one or more of these other medicines.
- If you are taking Mycobutin® (rifabutin), your healthcare provider may lower the dose of Mycobutin.
- If you are taking Dilantin® (phenytoin), your healthcare provider will need to monitor the levels of phenytoin in your blood and may need to adjust the dose of phenytoin.
- Other Special considerations
  VIRACEPT Oral Powder contains aspartame, a low-calorie sweetener, and therefore should not be taken by children with phenylketonuria (PKU).

What are the possible side effects of VIRACEPT?

- This list of side effects is not complete. If you have questions about side effects, ask your healthcare provider, nurse, or pharmacist. You should report any new or continuing symptoms to your healthcare provider right away. Your healthcare provider may be able to help you manage these side effects. Most of the side effects experienced with VIRACEPT have been mild to moderate.
- Diarrhea is the most common side effect in people taking VIRACEPT, and most adult patients had at least mild diarrhea at some point during treatment. In clinical studies, about 15–20% of patients receiving VIRACEPT 750 mg (three 250 mg tablets) three times daily or 1250 mg (five 250 mg tablets or two 625 mg tablets) two times daily had four or more loose stools a day. In most cases, VIRACEPT-associated diarrhea can be controlled using antidiarrheal medicines, such as Imodium A-D® (loperamide).
- Other side effects that occurred in 3–7% of patients receiving VIRACEPT include nausea, gas, and rash.
- The side effects observed in children and adults receiving VIRACEPT are similar. Diarrhea was also the most common side effect seen in children. Some children experienced low white blood cells (leukopenia/neutropenia), which resolved without treatment interruption in most cases.
- Diabetes and high blood sugar (hyperglycemia) occur in patients taking protease inhibitors such as VIRACEPT. Some patients had diabetes before starting protease inhibitors, others did not. Some patients needed changes in their diabetes medicine. Others needed new diabetes medicine after starting their VIRACEPT medicine.
- Changes in body fat have been seen in some patients taking antiretroviral therapy. These changes may include increased amount of fat in the upper back and neck ("buffalo hump"), breast and around the trunk. Loss of fat from the legs, arms and face may also happen. The cause and long-term health effects of these conditions are not known at this time.
- Some patients with hemophilia have increased bleeding with protease inhibitors.
- There were other side effects, some of them serious, noted in clinical studies that occurred in less than 2% of patients receiving VIRACEPT. However, these side effects may have been due to other drugs that patients were taking or to the illness itself. Except for diarrhea, there were not many differences in side effects in patients who took VIRACEPT along with other drugs compared with those who took only the other drugs.
- Before you start using any medicine, talk with your healthcare provider about what to expect and discuss ways to reduce the side effects you may have.

How should VIRACEPT be stored?

- Keep VIRACEPT and all other medicines out of the reach of children.
- Keep bottle closed and store at room temperature (between 59°F and 86°F) away from sources of moisture such as a sink or other damp place. Heat and moisture may reduce the effectiveness of VIRACEPT.
- Do not keep medicine that is out of date or that you no longer need. Be sure that if you throw any medicine away, it is out of the reach of children.
- Store in original container.

General advice about prescription medicines

Discuss all questions about your health with your healthcare provider. If you have questions about VIRACEPT or any other medication you are taking, ask your doctor, nurse, pharmacist, or other healthcare provider. You can also call 800-438-1985 toll free.

VIRACEPT and Agouron are registered trademarks of Agouron Pharmaceuticals, Inc.

Trademarks are the property of their respective owners.

AGOURON PHARMACEUTICALS, INC.
La Jolla, CA 92037, USA

LAB-0346-8.0

February 2011

PRINCIPAL DISPLAY PANEL - 250 mg Bottle Label

NDC 63010-010-30
300 Tablets

VIRACEPT®
(nelfinavir mesylate)
Tablets

Each tablet contains nelfinavir mesylate
equivalent to 250 mg of nelfinavir (free base).

ALERT: Find out about
medicines that should NOT
be taken with VIRACEPT.

Note to Pharmacist: Do not
cover ALERT box with
pharmacy label.

Rx only

250 mg

Agouron®
Pharmaceuticals, Inc.
A Pfizer Company

300 Tablets

Repacked by:

H.J. Harkins Company, Inc.

Grover Beach, CA 93433